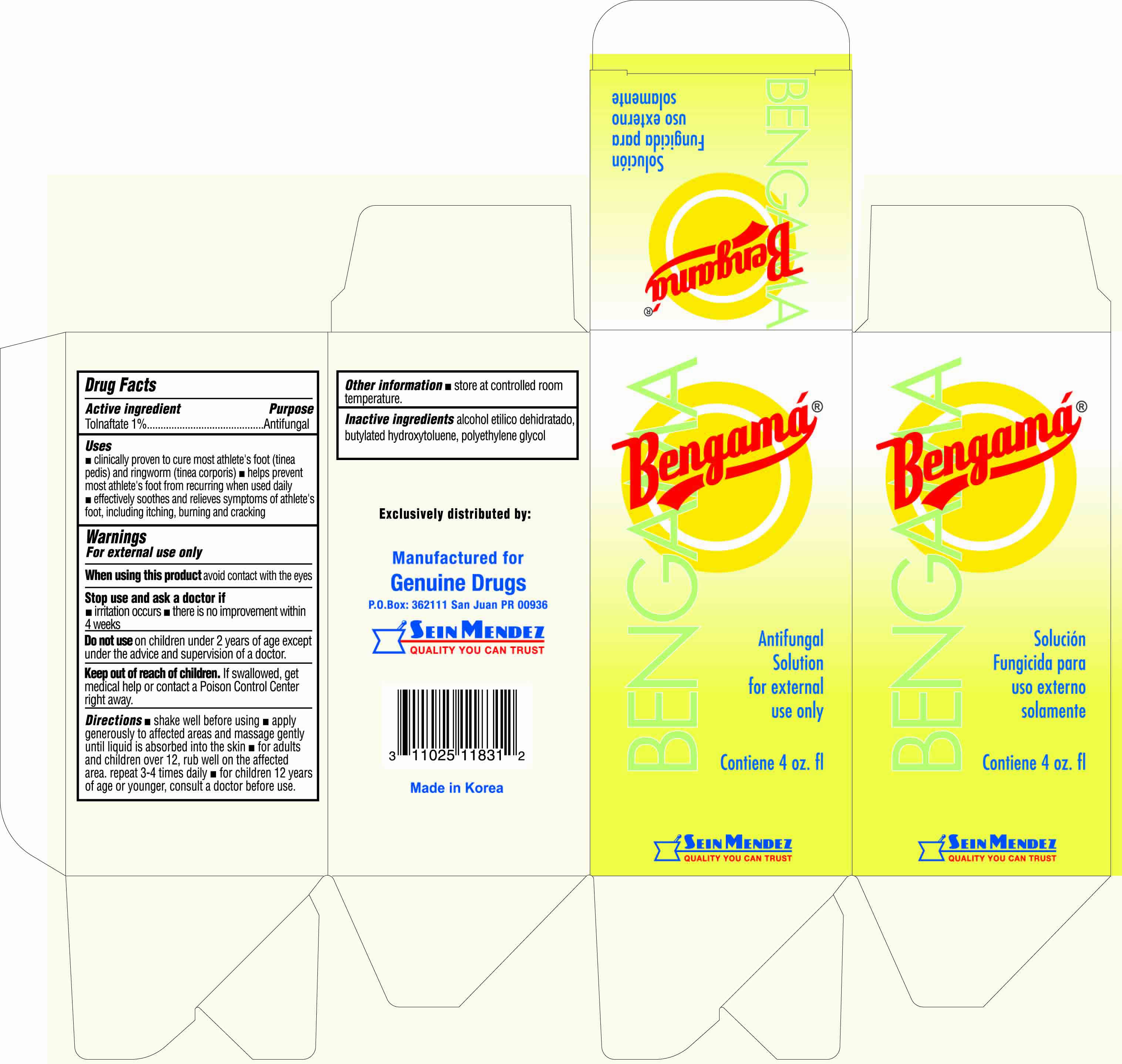 DRUG LABEL: Bengama Antifungal
NDC: 69666-831 | Form: SOLUTION
Manufacturer: Genuine Drugs
Category: otc | Type: HUMAN OTC DRUG LABEL
Date: 20230217

ACTIVE INGREDIENTS: TOLNAFTATE 1 mg/100 mL
INACTIVE INGREDIENTS: BUTYLATED HYDROXYTOLUENE; POLYETHYLENE GLYCOL, UNSPECIFIED

Bengama Antifungal Solution

Active ingredient (in each gram)

Tolnaftate 1%

Purpose

Antifungal

Uses

- clinically proven to cure most athlete's foot (tinea pedis) and ringworm (tinea corporis)
- helps prevnet most athlete's foot from recurring when used daily
- effectively soothes and relieves symptoms of athlete's foot, including itching, burning and cracking

Warnings

For external use only

When using this product

avoid contact with the eyes

Stop use and ask a doctor if

- irritation occurs
- there is no improvement within 4 weeks

Do not use

on children under 2 years of age except under the advice and supervision of a doctor.

Keep out of reach of children.

If swallowed, get medical help or contact a Poison Control Center right away.

Directions

- shake well before using
- apply generously to affected areas and massage gently until liquid is absorbed into the skin
- for adults and children over 12, rub well on the afffected area. repeat 3-4 times daily
- for children 12 years of age or younger, consult a doctor before use

Inactive ingredients

dehydrated ethyl alcohol, butylated hydroxytoluene, polyethylene glycol

Other information

- store at controlled room temperature

Package label

Bengama antifungal